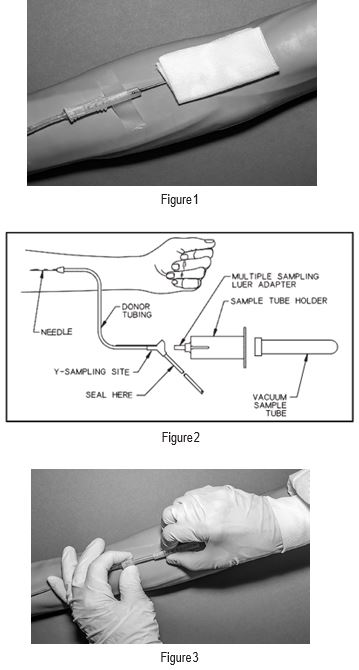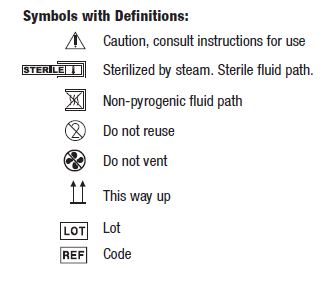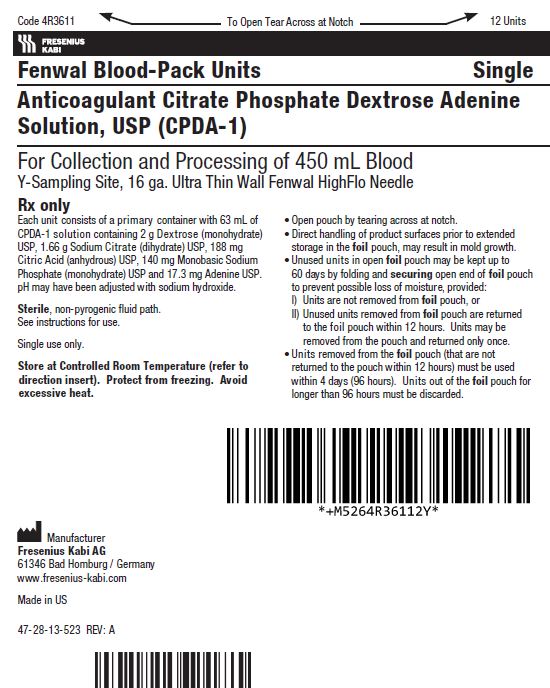 DRUG LABEL: CPDA-1
NDC: 0942-9394 | Form: SOLUTION
Manufacturer: Fenwal, Inc.
Category: prescription | Type: HUMAN PRESCRIPTION DRUG LABEL
Date: 20221101

ACTIVE INGREDIENTS: DEXTROSE MONOHYDRATE 2 g/63 mL; TRISODIUM CITRATE DIHYDRATE 1.66 g/63 mL; ANHYDROUS CITRIC ACID 188 mg/63 mL; SODIUM PHOSPHATE, MONOBASIC, MONOHYDRATE 140 mg/63 mL; ADENINE 17.3 mg/63 mL
INACTIVE INGREDIENTS: SODIUM HYDROXIDE

Anticoagulant Citrate Phosphate Dextrose Adenine Solution, USP (CPDA-1) BLOOD-PACK™ Unit

Fenwal Blood-Pack Units
Rx only
Using Anticoagulant Citrate Phosphate Dextrose Adenine Solution, USP (CPDA-1) and Fenwal HighFlo Needle

Contains Y Sampling Site for the collection of unanticoagulated whole blood samples for laboratory testing.

Instructions for Use
Collection Procedure:
Use aseptic technique
Note: Nominal tubing dimensions of product are 0.118" inner diameter x 0.025" wall thickness.
Note: If the Y-Sampling Site is not used, donor samples may be collected using an alternate method following standard procedures.
Precautions:
• Do not use unless the solution is clear.
• Before beginning procedure, obtain one access device for each Blood-Pack unit with Y-Sampling Site to be processed.
1. Identify Blood-Pack unit using appropriate donor identification system.
2. Adjust donor scale to desired collection weight and position primary container on the donor scale as far as possible below donor arm.
3. Clamp donor tubing between Fenwal HighFlo1 needle and primary container. This step may be performed prior to step 1 or 2.
4. Following blood center procedures, apply pressure to donor's arm and disinfect site of venipuncture.
5. Remove needle cover per instructions below:
a) Holding the hub and cover near the tamper-evident seal, twist cover and hub in opposite directions to break seal.
b) Remove needle cover, being careful not to drag the cover across the needle point.
6. Following blood center procedures, perform venipuncture, appropriately secure donor needle and/or tubing and release clamp on donor tubing.
7. When good blood flow is established, stabilize the front of the needle guard to arm with tape. (see Figure 1)
8. Mix blood and anticoagulant in primary container at several intervals during collection and immediately after collection.
9. Collect the appropriate volume based on Blood-Pack unit used.
Note: The volume of anticoagulant is sufficient for the blood collection indicated on Blood-Pack unit ± 10%.
10. Release the pressure on the donor's arm as appropriate.
Precaution: Do not proceed with the remaining steps until the entire whole blood unit is collected.
11. To avoid possible contamination of the whole blood unit, before filling whole blood sample tubes, hermetically seal the donor tubing near the
Y-Sampling Site on the side leading to the primary container using
a metal clip or appropriate alternate method.
Precaution: Complete steps 12 - 20 within approximately 4 minutes after sealing the donor tubing to avoid possible clot formation in the tubing.
12. To collect samples, insert the access device by pushing firmly into the Y-Sampling Site until the membrane seal is penetrated (see Figure 2).
Note: If the access device is assembled such that the outer barrel is screwed onto the Luer, make sure to rotate clockwise upon insertion to avoid barrel detaching from Luer.
13. Open the cap on the access device (if applicable).
14. Directly align the vacuum sample tube with the internal needle in the access device. Insert vacuum sample tube into device until the stopper is punctured.
15. Allow vacuum sample tube to fill with blood then remove from the access device.
16. Repeat steps 14 and 15 until the desired number of vacuum sample tubes have been filled.
Notes:
• If the access device needs to be replaced, clamp the tubing between the needle and the Y-Sampling Site. Then, grasp base of Sampling Site with one hand and pull the access device out with the other hand. Firmly insert the new access device. Remove clamp and continue sampling.
• If the access device is assembled such that the outer barrel is screwed onto the Luer, make sure to rotate clockwise upon removal to avoid barrel detaching from Luer.
• The access device can only be replaced one time.
Precaution: When replacing the access device, be careful to avoid contact with any blood droplets on the Luer or Sampling Site. Discard used access device appropriately.
17. Release remaining pressure on donor's arm.
18. If desired, apply clamp to donor tubing between needle and Y-Sampling Site.
19. Withdrawal of Needle (see Figure 3)
Precaution: The needle guard must be held stationary while the needle is withdrawn into it.
a) Place folded sterile gauze over puncture site and hold in place with finger tip without exerting pressure.
b) Hold sides of the needle guard near the front, between the index finger and thumb. Pull the hub back smoothly until the needle is completely enclosed and securely locked into the needle guard.
c) Confirm the needle is completely enclosed and securely locked into the needle guard.
20. Strip blood from donor tubing into primary container, mix and allow the tubing to refill; repeat once. Seal at X marks on donor tubing to provide numbered aliquots of anticoagulated blood for typing or crossmatching.
Note: Step 21 may be performed prior to step 20 if desired.
21. Remove and discard the Y-Sampling Site and the needle into an appropriate biohazardous waste container following established procedures.
22. Store suspended CPDA-1 Whole Blood/Red Blood Cells between 1 and 6°C.
23. Infuse CPDA-1 Whole Blood/Red Blood Cells within 35 days of collection.

Store at Controlled Room Temperature. Protect from freezing. Avoid excessive heat.
Definition of "Controlled Room Temperature":
"A temperature maintained thermostatically that encompasses the usual and customary working environment of 20° to 25°C (68° to 77°F); that results in a mean kinetic temperature calculated to be not more than 25°C; and that allows for excursions between 15°C and 30°C (59° and 86°F) that are experienced in pharmacies, hospitals, and warehouses. Provided the mean kinetic temperature remains in the allowed range, transient spikes up to 40°C are permitted as long as they do not exceed 24 hours ... The mean kinetic temperature is a calculated value that may be used as an isothermal storage temperature that simulates the non isothermal effects of storage temperature variations."

Reference: United States Pharmacopeia, General Notices. United States Pharmacopeial Convention, Inc. 12601 Twinbrook Parkway, Rockville, MD.

^1 Van der Meer, P.F., & de Korte, D. “Increase of blood donation speed by optimizing the needle-to-tubing connection: an application of donation software.” Vox Sanguinis 2009, 97: 21-25

Manufacturer
Fresenius Kabi AG
61346 Bad Homburg / Germany
www.fresenius-kabi.com
1-800-933-6925

47-23-13-513 REV: A

© 2019 Fresenius Kabi AG. All rights reserved

PACKAGE/LABEL DISPLAY PANEL

Code 4R3611

12 Units

FRESENIUS KABI
Fenwal Blood-Pack Units
Single

Anticoagulant Citrate Phosphate Dextrose Adenine Solution, USP (CPDA-1)

For the Collection and Processing of 450 mL Blood

Y-Sampling Site, 16 ga. Ultra Thin Wall Fenwal HighFlo Needle

Rx only

Each unit consists of a primary container with 63 mL of CPDA-1 solution containing 2 g Dextrose (monohydrate) USP, 1.66 g Sodium Citrate (dihydrate) USP, 188 mg Citric Acid (anhydrous) USP, 140 mg Monobasic Sodium Phosphate (monohydrate) USP and 17.3 mg Adenine USP. pH may have been adjusted with sodium hydroxide.

Sterile, non-pyrogenic fluid path.
See instructions for use.

Single use only.
Store at Controlled Room Temperature (refer to direction insert). Protect from freezing. Avoid excessive heat.

Open pouch by tearing across at notch.
Direct handling of product surfaces prior to extended storage in the foil pouch, may result in mold growth.
Unused units in open foil pouch may be kept up to 60 days by folding and securing open end of foil pouch to prevent possible loss of moisture, provided:

  - Units are not removed from foil pouch, or
  - Unused units removed from foil pouch are returned to the foil pouch within 12 hours. Units may be removed from the pouch and returned only once.
Units removed from the foil pouch (that are not returned to the pouch within 12 hours) must be used within 4 days (96 hours). Units out of the foil pouch for longer than 96 hours must be discarded.

Manufacturer
Fresenius Kabi AG
61346 Bad Homburg / Germany
www.fresenius-kabi.com
Made in US

47-28-13-523 REV: A